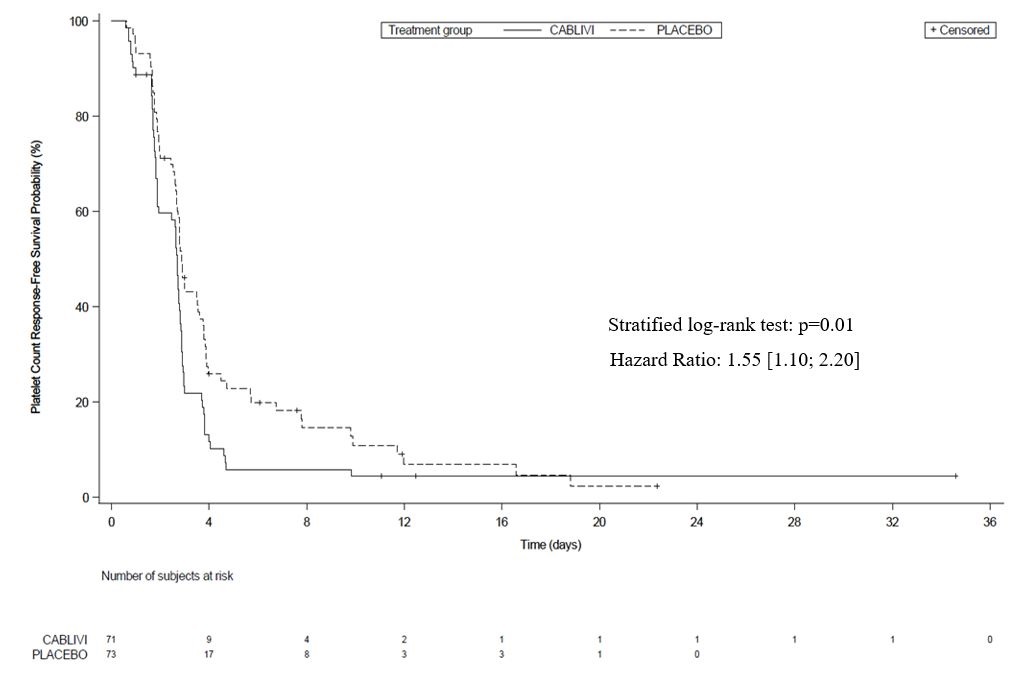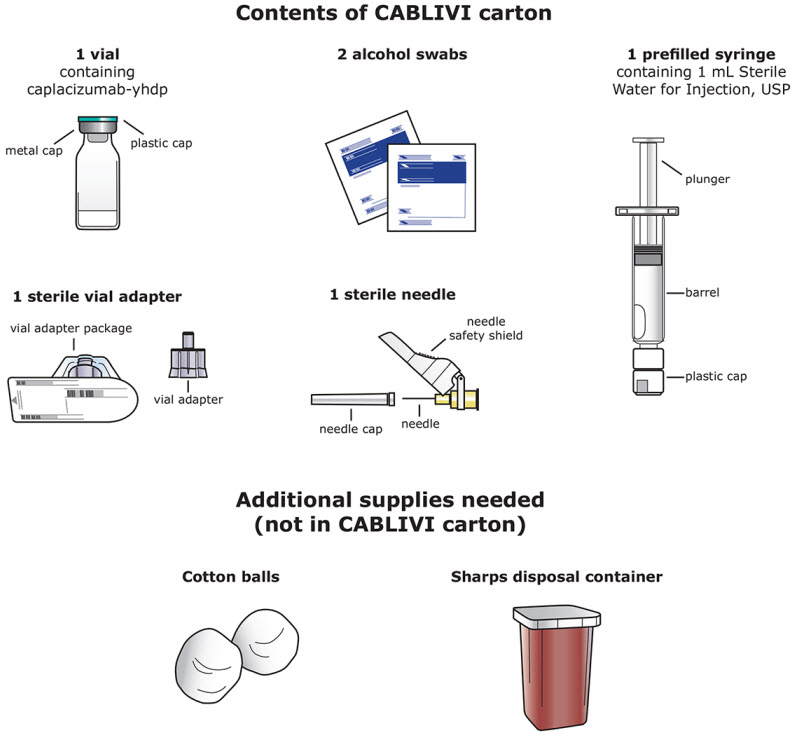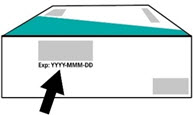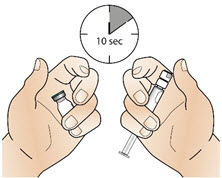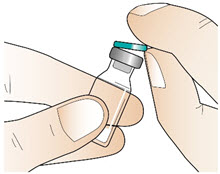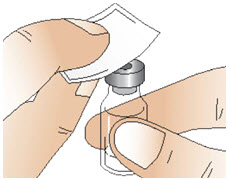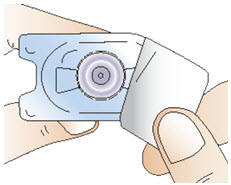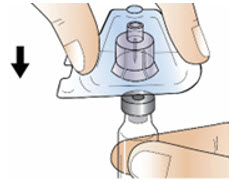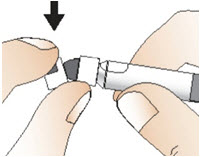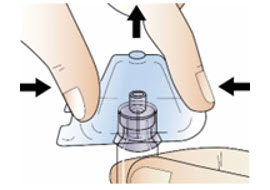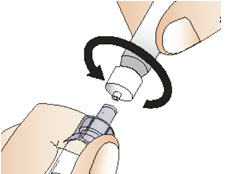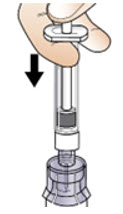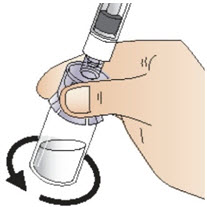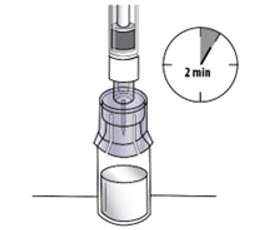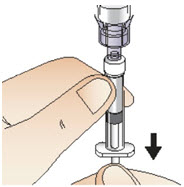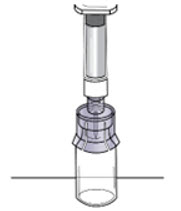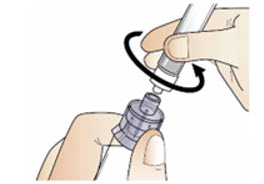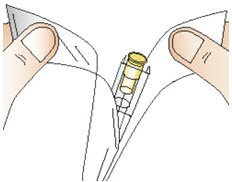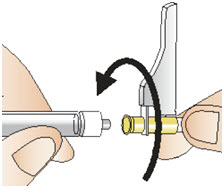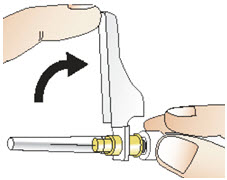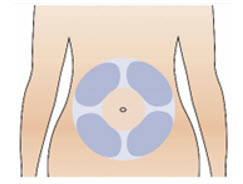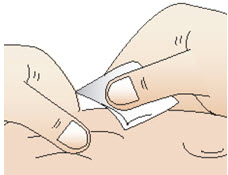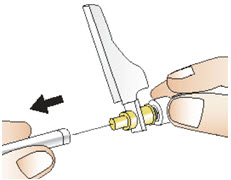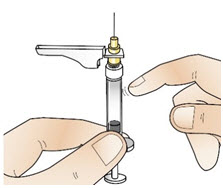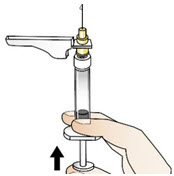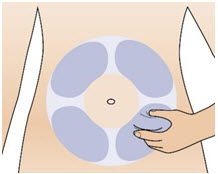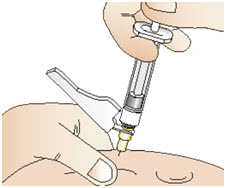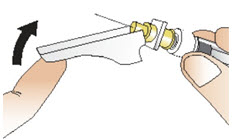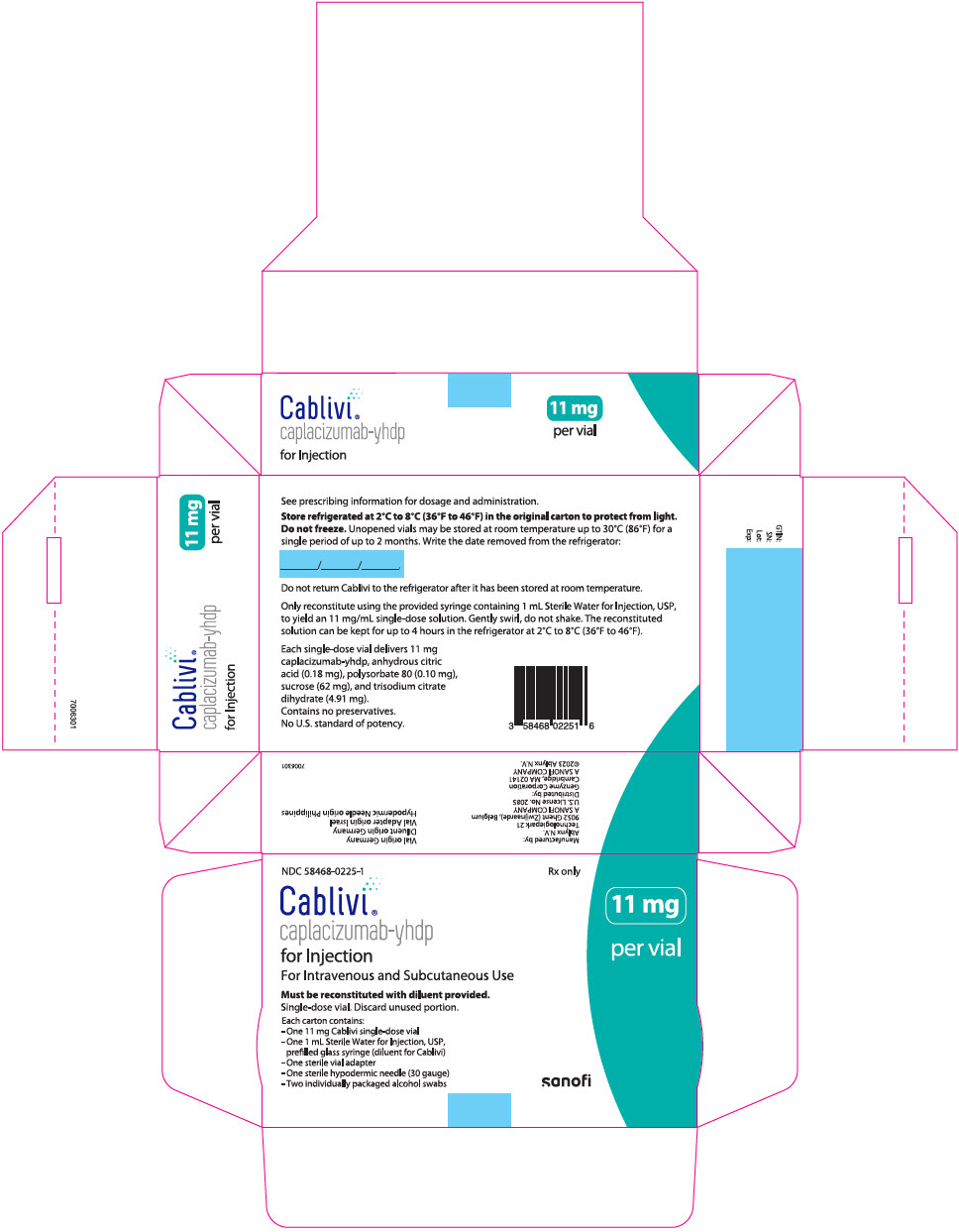 DRUG LABEL: Cablivi
NDC: 58468-0225 | Form: KIT | Route: INTRAVENOUS
Manufacturer: Genzyme Corporation
Category: prescription | Type: HUMAN PRESCRIPTION DRUG LABEL
Date: 20241104

ACTIVE INGREDIENTS: CAPLACIZUMAB 11 mg/1 mL
INACTIVE INGREDIENTS: ANHYDROUS CITRIC ACID 0.18 mg/1 mL; POLYSORBATE 80 0.1 mg/1 mL; SUCROSE 62 mg/1 mL; TRISODIUM CITRATE DIHYDRATE 4.91 mg/1 mL; WATER

HIGHLIGHTS OF PRESCRIBING INFORMATION

These highlights do not include all the information needed to use CABLIVI® safely and effectively. See full prescribing information for CABLIVI.
CABLIVI (caplacizumab-yhdp) for injection, for intravenous or subcutaneous use
Initial U.S. Approval: 2019

1 INDICATIONS AND USAGE

CABLIVI is a von Willebrand factor (vWF)-directed antibody fragment indicated for the treatment of adult patients with acquired thrombotic thrombocytopenic purpura (aTTP), in combination with plasma exchange and immunosuppressive therapy. (1)

2 DOSAGE AND ADMINISTRATION

- CABLIVI should be administered upon the initiation of plasma exchange therapy. The recommended dose of CABLIVI is as follows: (2.1)
  - First day of treatment: 11 mg bolus intravenous injection at least 15 minutes prior to plasma exchange followed by an 11 mg subcutaneous injection after completion of plasma exchange on day 1.
  - Subsequent treatment during daily plasma exchange: 11 mg subcutaneous injection once daily following plasma exchange.
  - Treatment after the plasma exchange period: 11 mg subcutaneous injection once daily for 30 days beyond the last plasma exchange.
  - If after initial treatment course, sign(s) of persistent underlying disease such as suppressed ADAMTS13 activity levels remain present, treatment may be extended for a maximum of 28 days.
  - Discontinue CABLIVI if the patient experiences more than 2 recurrences of aTTP, while on CABLIVI.
- The first dose should be administered by a healthcare provider as a bolus intravenous injection. Administer subsequent doses subcutaneously in the abdomen. (2.3)

3 DOSAGE FORMS AND STRENGTHS

For injection: 11 mg as a lyophilized powder in a single-dose vial. (3)

4 CONTRAINDICATIONS

Previous severe hypersensitivity reaction to caplacizumab-yhdp or any of the excipients. (4)

5 WARNINGS AND PRECAUTIONS

Hemorrhage: Serious and fatal bleeding can occur. Risk of bleeding is increased in patients with underlying coagulopathies or on concomitant antiplatelet agents or anticoagulants. If clinically significant bleeding occurs, interrupt treatment. Withhold CABLIVI 7 days prior to elective surgery, dental procedures, or other invasive interventions. (5.1)

6 ADVERSE REACTIONS

Most common adverse reactions (incidence >15%) are epistaxis, headache, and gingival bleeding. (6.1)

To report SUSPECTED ADVERSE REACTIONS, contact Ablynx US at 1-800-745-4447 or FDA at 1-800-FDA-1088 or www.fda.gov/medwatch.

7 DRUG INTERACTIONS

Concomitant use of anticoagulants or antiplatelet agents with CABLIVI may increase the risk of bleeding. Monitor closely for bleeding with concomitant use. (7)

FULL PRESCRIBING INFORMATION

1 INDICATIONS AND USAGE

CABLIVI is indicated for the treatment of adult patients with acquired thrombotic thrombocytopenic purpura (aTTP), in combination with plasma exchange and immunosuppressive therapy.

2 DOSAGE AND ADMINISTRATION

2.1 Recommended Dose and Schedules

CABLIVI should be administered upon initiation of plasma exchange therapy. The recommended dose of CABLIVI is as follows:

- First day of treatment: 11 mg bolus intravenous injection at least 15 minutes prior to plasma exchange followed by an 11 mg subcutaneous injection after completion of plasma exchange on day 1.
- Subsequent days of treatment during daily plasma exchange: 11 mg subcutaneous injection once daily following plasma exchange.
- Treatment after plasma exchange period: 11 mg subcutaneous injection once daily continuing for 30 days following the last daily plasma exchange. If after initial treatment course, sign(s) of persistent underlying disease such as suppressed ADAMTS13 activity levels remain present, treatment may be extended for a maximum of 28 days.

Discontinue CABLIVI if the patient experiences more than 2 recurrences of aTTP, while on CABLIVI.

Avoid concomitant use of antiplatelet agents or anticoagulants [see Warnings and Precautions (5.1)].

Missed Dose

If a dose of CABLIVI is missed during the plasma exchange period, it should be given as soon as possible. If a dose of CABLIVI is missed after the plasma exchange period, it can be administered within 12 hours of the scheduled time of administration. Beyond 12 hours, the missed dose should be skipped and the next daily dose administered according to the usual dosing schedule.

2.2 Discontinuation for Surgery and Other Interventions

Withhold CABLIVI treatment 7 days prior to elective surgery, dental procedures, or other invasive interventions [see Warnings and Precautions (5.1)].

2.3 Reconstitution and Administration Instructions

The first dose of CABLIVI should be administered by a healthcare provider as a bolus intravenous injection. Administer subsequent doses subcutaneously in the abdomen. Avoid injections around the navel. Do not administer consecutive injections in the same abdominal quadrant.

Patients or caregivers may inject CABLIVI subcutaneously after proper training on the preparation and administration of CABLIVI, including aseptic technique [see Instructions for Use].

- Ensure the CABLIVI vial and diluent syringe are at room temperature.
- Reconstitute CABLIVI before administration using the provided syringe containing 1 mL Sterile Water for Injection, USP, to yield an 11 mg/mL single-dose solution.
- Using aseptic technique throughout the preparation of the solution, attach the vial adapter to the vial containing CABLIVI.
- Remove the plastic cap from the syringe and attach it to the vial adapter by twisting it clockwise until it cannot twist any further.
- Slowly push the syringe plunger down until the syringe is empty. Do not remove the syringe from the vial adapter.
- Gently swirl the vial until the cake or powder is completely dissolved. Do not shake.
- Visually inspect that the reconstituted solution is clear and colorless.
- Withdraw all of the clear, colorless reconstituted solution from the vial into the syringe. Label the CABLIVI syringe.
- Administer the full amount of reconstituted solution.
- For the initial intravenous injection, if using an intravenous line, the glass syringe should be connected to a standard Luer lock (and not a needleless connector) and flushed with either 0.9% Sodium Chloride Injection, USP, or 5% Dextrose Injection, USP.
- Use the CABLIVI solution immediately. If not, use CABLIVI within 4 hours after reconstitution when stored in the refrigerator at 2°C to 8°C (36°F to 46°F).

3 DOSAGE FORMS AND STRENGTHS

For injection: 11 mg as a white lyophilized powder in a single-dose vial.

4 CONTRAINDICATIONS

CABLIVI is contraindicated in patients with a previous severe hypersensitivity reaction to caplacizumab-yhdp or to any of the excipients. Hypersensitivity reactions have included urticaria [see Adverse Reactions (6.1)].

5 WARNINGS AND PRECAUTIONS

5.1 Hemorrhage

CABLIVI increases the risk of bleeding [see Adverse Reactions (6.1)].

In clinical studies, severe bleeding adverse reactions of epistaxis, gingival bleeding, upper gastrointestinal hemorrhage, and metrorrhagia were each reported in 1% of subjects. Overall, bleeding events occurred in approximately 58% of patients on CABLIVI versus 43% of patients on placebo.

In the postmarketing setting, cases of life-threatening and fatal bleeding were reported in patients receiving CABLIVI.

The risk of bleeding is increased in patients with underlying coagulopathies (e.g. hemophilia, other coagulation factor deficiencies). It is also increased with concomitant use of CABLIVI with drugs affecting hemostasis and coagulation [see Drug Interactions (7) and Clinical Pharmacology (12.3)].

Avoid concomitant use of CABLIVI with antiplatelet agents or anticoagulants. Interrupt use of CABLIVI if clinically significant bleeding occurs. If needed, von Willebrand factor concentrate may be administered to rapidly correct hemostasis. If CABLIVI is restarted, monitor closely for signs of bleeding.

Withhold CABLIVI for 7 days prior to elective surgery, dental procedures or other invasive interventions. If emergency surgery is needed, the use of von Willebrand factor concentrate may be considered to correct hemostasis. After the risk of surgical bleeding has resolved, and CABLIVI is resumed, monitor closely for signs of bleeding.

6 ADVERSE REACTIONS

The following clinically significant adverse reactions are also discussed in other sections of the labeling:

- Hemorrhage [see Warnings and Precautions (5.1)]

6.1 Clinical Trials Experience

Because clinical trials are conducted under widely varying conditions, adverse reaction rates observed in the clinical trials of a drug cannot be directly compared to rates in the clinical trials of another drug and may not reflect the rates observed in practice.

The safety of CABLIVI was evaluated in two placebo-controlled clinical studies (HERCULES, in which 71 patients received CABLIVI; and TITAN, in which 35 patients received CABLIVI). The data described below and in the Warnings and Precautions reflect exposure to CABLIVI during the blinded periods of both studies, which include 106 patients with aTTP who received at least one dose, age 18 to 79 years, of whom 69% were female and 73% were White. The median treatment duration with CABLIVI was 35 days (range 1–77 days).

The most frequently reported adverse reactions (>15%) were epistaxis, headache and gingival bleeding. Seven patients (7%) in the CABLIVI group experienced an adverse reaction leading to study drug discontinuation. None of the adverse reactions leading to discontinuation were observed in more than 1% of patients.

Among 106 patients treated with CABLIVI during the TITAN and HERCULES studies, serious bleeding adverse reactions reported in ≥2% patients included epistaxis (4%) and subarachnoid hemorrhage (2%).

Adverse reactions that occurred in ≥2% of patients treated with CABLIVI and more frequently than in those treated with placebo across the pooled data from the two trials are summarized in Table 1. Urticaria was seen during plasma exchange.

Table 1: Adverse Reactions in ≥2% of Patients Treated with CABLIVI and More Frequent than Placebo During the Blinded Periods of aTTP Studies (HERCULES and TITAN)
Adverse Reaction by Body System | CABLIVI (N=106) n (%) | Placebo (N=110) n (%)
Gastrointestinal disorders
Gingival bleeding | 17 (16) | 3 (3)
Rectal hemorrhage | 4 (4) | 0 (0)
Abdominal wall hematoma | 3 (3) | 1 (1)
General disorders and administration site conditions
Fatigue | 16 (15) | 10 (9)
Pyrexia | 14 (13) | 12 (11)
Injection site hemorrhage | 6 (6) | 1 (1)
Catheter site hemorrhage | 6 (6) | 5 (5)
Injection site pruritus | 3 (3) | 0 (0)
Musculoskeletal and connective tissue disorders
Back pain | 7 (7) | 4 (4)
Myalgia | 6 (6) | 2 (2)
Nervous system disorders
Headache | 22 (21) | 15 (14)
Paresthesia | 13 (12) | 11 (10)
Renal and urinary disorders
Urinary tract infection | 6 (6) | 4 (4)
Hematuria | 4 (4) | 3 (3)
Reproductive system and breast disorders
Vaginal hemorrhage | 5 (5) | 2 (2)
Menorrhagia | 4 (4) | 1 (1)
Respiratory, thoracic and mediastinal disorders
Epistaxis | 31 (29) | 6 (6)
Dyspnea | 10 (9) | 5 (5)
Skin and subcutaneous tissue disorders
Urticaria | 15 (14) | 7 (6)

6.2 Immunogenicity

As with all therapeutic proteins, there is potential for immunogenicity. The detection of antibody formation is highly dependent on the sensitivity and specificity of the assay. Additionally, the observed incidence of antibody (including neutralizing antibody) positivity in an assay may be influenced by several factors including assay methodology, sample handling, timing of sample collection, concomitant medications, and underlying disease. For these reasons, comparison of the incidence of antibodies to caplacizumab-yhdp in the studies described below, with the incidence of antibodies in other studies, or to other products, may be misleading.

The prevalence of pre-existing antibodies binding to caplacizumab-yhdp observed during clinical studies and during evaluation of commercially available human samples varied between 4% and 63%. In aTTP patients, pre-existing antibodies can be produced by the patient or can originate from donor plasma during plasma exchange. No clinically apparent impact of these pre-existing antibodies on clinical efficacy or safety was found. Treatment-emergent anti-drug antibodies (TE ADA) against caplacizumab-yhdp were detected in 3% of patients treated with CABLIVI in the HERCULES study. In the HERCULES study, TE ADA were further characterized as having neutralizing potential. There was no clinically apparent impact on clinical efficacy or safety [see Clinical Pharmacology (12.3)].

6.3 Postmarketing Experience

The following adverse reactions have been identified during postapproval use of CABLIVI. Because these reactions are reported voluntarily from a population of uncertain size, it is not always possible to reliably estimate their frequency or establish a causal relationship to caplacizumab-yhdp exposure.

General disorders and administration site conditions:

Injection site reactions including injection site pain, injection site bruising and injection site erythema

7 DRUG INTERACTIONS

Concomitant Use of Anticoagulants or Antiplatelet Agents

Concomitant use of CABLIVI with any anticoagulant or antiplatelet agent may increase the risk of bleeding. Avoid concomitant use when possible. Assess and monitor closely for bleeding with concomitant use [see Warnings and Precautions (5.1) and Clinical Pharmacology (12.3)].

8 USE IN SPECIFIC POPULATIONS

8.1 Pregnancy

Risk Summary

There are no available data on CABLIVI use in pregnant women to inform a drug-associated risk of major birth defects and miscarriage. However, there are potential risks of hemorrhage in the mother and fetus associated with use of CABLIVI (see Clinical Considerations). In animal reproduction studies, there was no evidence of adverse developmental outcomes with intramuscular administration of caplacizumab-yhdp during organogenesis in guinea pigs at exposures approximately 30 times the AUC in humans at the recommended subcutaneous injection dose of 11 mg (see Data).

All pregnancies have a background risk of birth defect, loss, or other adverse outcomes. The background rate of major birth defects and miscarriage in the indicated population is unknown. In the U.S. general population, the estimated background rate of major birth defects and miscarriage in clinically recognized pregnancies is 2% to 4% and 15% to 20%, respectively.

Clinical Considerations

Fetal/neonatal adverse reactions

CABLIVI may increase the risk of bleeding in the fetus and neonate. Monitor neonates for bleeding [see Warnings and Precautions (5.1)].

Maternal adverse reactions

All patients receiving CABLIVI, including pregnant women, are at risk for bleeding. Pregnant women receiving CABLIVI should be carefully monitored for evidence of excessive bleeding [see Warnings and Precautions (5.1)].

Data

Animal data

Two separate reproduction studies were conducted in pregnant guinea pigs with administration of caplacizumab-yhdp during the organogenesis period.

In an embryo-fetal development study, caplacizumab-yhdp was administered intramuscularly at doses up to 20 mg/kg/day from gestational day (GD) 6 to GD 41 in guinea pigs. No maternal toxicity or adverse developmental outcomes were observed.

In a toxicokinetic study assessing the exposure of caplacizumab-yhdp in the dams and fetuses, caplacizumab-yhdp was administered once daily to female guinea pigs at doses up to 40 mg/kg/day (corresponding to a drug exposure of approximately 30 times the AUC in humans at the recommended dose of 11 mg) by intramuscular injection from GD 6 to GD 41 or GD 61. Exposure to caplacizumab-yhdp was observed in the dams and fetuses, with no effects on embryo-fetal development.

8.2 Lactation

Risk Summary

There is no information regarding the presence of caplacizumab-yhdp in human milk, the effects on the breastfed child or the effects on milk production.

The developmental and health benefits of breastfeeding should be considered along with the mother's clinical need for CABLIVI and any potential adverse effects on the breastfed child from CABLIVI, or from the underlying maternal condition.

8.4 Pediatric Use

The safety and effectiveness of CABLIVI in pediatric patients have not been established.

8.5 Geriatric Use

Clinical studies of CABLIVI did not include sufficient numbers of subjects aged 65 and over to determine whether they respond differently from younger subjects.

8.6 Hepatic Impairment

No formal studies with CABLIVI have been conducted in patients with severe acute or chronic hepatic impairment and no data regarding the use of CABLIVI in these populations are available. Due to a potential increased risk of bleeding, use of CABLIVI in patients with severe hepatic impairment requires close monitoring for bleeding [see Warnings and Precautions (5.1)].

10 OVERDOSAGE

In case of overdose, based on the pharmacological action of CABLIVI, there is the potential for an increased risk of bleeding [see Warnings and Precautions (5.1)]. Close monitoring for signs and symptoms of bleeding is recommended. If needed, the use of von Willebrand factor concentrate could be considered to correct hemostasis.

11 DESCRIPTION

Caplacizumab-yhdp is a von Willebrand factor (vWF)-directed antibody fragment that consists of two identical humanized building blocks, linked by a three-alanine linker. Caplacizumab-yhdp is produced in Escherichia coli by recombinant DNA technology and has an approximate molecular weight of 28 kDa.

CABLIVI (caplacizumab-yhdp) for injection is a sterile, white, preservative-free, lyophilized powder. Each single-dose vial delivers 11 mg caplacizumab-yhdp, anhydrous citric acid (0.18 mg), polysorbate 80 (0.10 mg), sucrose (62 mg), and trisodium citrate dihydrate (4.91 mg). After reconstitution with 1 mL of Sterile Water for Injection, USP, the final concentration is 11 mg/mL, at a pH of approximately 6.5.

12 CLINICAL PHARMACOLOGY

12.1 Mechanism of Action

Caplacizumab-yhdp targets the A1-domain of vWF, and inhibits the interaction between vWF and platelets, thereby reducing both vWF-mediated platelet adhesion and platelet consumption.

12.2 Pharmacodynamics

Ristocetin cofactor (RICO) activity was used to assess vWF activity. Subcutaneous doses of caplacizumab-yhdp at greater than or equal to the approved recommended dosage to healthy subjects and patients with aTTP decreased RICO activity levels to below 20% approximately 4 hours post-dose. RICO activity returned to baseline values within 7 days of drug discontinuation.

Caplacizumab-yhdp decreased vWF antigen and factor VIII:C levels. These reductions were transient and returned to baseline upon cessation of treatment.

12.3 Pharmacokinetics

Caplacizumab-yhdp pharmacokinetics depends on the expression of the target vWF and are not dose proportional. Higher levels of vWF antigen increase the fraction of drug-target complex retained in the circulation. Steady-state was reached following the first administration of CABLIVI in healthy subjects, with minimal accumulation. Following a single subcutaneous dose of 10 mg caplacizumab-yhdp to healthy subjects the mean (CV%) peak concentration (Cmax) was 528 (20%) ng/mL and AUC0–24 was 7951 (16%). Following subcutaneous dosing of 10 mg caplacizumab-yhdp daily for 14 days to healthy subjects, the mean (CV%) Cmax was 348 (30%) ng/mL and AUC0–τ was 6808 (26%) hr∙ng/mL.

Absorption

The bioavailability of subcutaneous caplacizumab-yhdp is approximately 90%.

The maximum concentration was observed 6 to 7 hours after subcutaneous dosing of 10 mg caplacizumab-yhdp once daily in healthy subjects.

Distribution

Caplacizumab-yhdp central volume of distribution is 6.33 L in patients with aTTP.

Elimination

The half-life of caplacizumab-yhdp is concentration and target-level dependent.

Metabolism

The available data suggest target-bound caplacizumab-yhdp is metabolized within the liver. Because caplacizumab-yhdp is a monoclonal antibody fragment, it is expected to be catabolized by various proteolytic enzymes.

Excretion

The available nonclinical data suggest unbound caplacizumab-yhdp is cleared renally.

Antidrug Antibodies

No clinically significant differences in the pharmacokinetics of caplacizumab-yhdp were observed in patients with pre-existing or treatment-emergent anti-drug antibodies.

Specific Populations

No clinically significant differences in the pharmacokinetics of caplacizumab-yhdp were observed based on age (18 to 79 years), sex (66% females), race (White [83%] and Black [17%]), blood group (O [41%] and other groups [59%]), or renal impairment (mild [CrCl: 60 to 90 mL/min], moderate [CrCl: 30 to 60 mL/min] or severe [CrCl: 15 to 30 mL/min]). The effect of hepatic impairment on the pharmacokinetics of caplacizumab-yhdp is unknown [see Use in Specific Populations (8.6)].

Drug Interaction Studies

No dedicated drug-drug interaction studies with caplacizumab-yhdp have been conducted.

13 NONCLINICAL TOXICOLOGY

13.1 Carcinogenesis, Mutagenesis, Impairment of Fertility

No studies have been performed to evaluate the potential of caplacizumab-yhdp for carcinogenicity or genotoxicity.

Animal reproduction studies assessing the effects of caplacizumab-yhdp on male and female fertility have not been conducted.

14 CLINICAL STUDIES

The efficacy of CABLIVI for the treatment of adult patients with acquired thrombotic thrombocytopenic purpura (aTTP) in combination with plasma exchange and immunosuppressive therapy was established in a pivotal multicenter, randomized, double-blind, placebo-controlled trial (HERCULES) (NCT02553317).

A total of 145 patients were enrolled in the HERCULES study; the median age was 45 (range: 18 to 79) years, 69% were female, 73% were White. Patients were randomized to either CABLIVI (n=72) or placebo (n=73). Patients in both groups received plasma exchange and immunosuppressive therapy. Patients were stratified according the severity of neurological involvement (Glasgow Coma Scale score ≤12 or 13 to 15). Patients with sepsis, infection with E. coli 0157, atypical hemolytic uremic syndrome, disseminated intravascular coagulation or congenital thrombotic thrombocytopenic purpura were not eligible for enrollment.

Patients received a single 11 mg CABLIVI bolus intravenous injection or placebo prior to the first plasma exchange on study, followed by a daily subcutaneous injection of 11 mg CABLIVI or placebo after completion of plasma exchange, for the duration of the daily plasma exchange period and for 30 days thereafter. If after the initial treatment course, sign(s) of persistent underlying disease such as suppressed ADAMTS13 activity levels remained present, treatment was extended for 7 day intervals for a maximum of 28 days.

The median treatment duration with CABLIVI was 35 days.

The clinical trial protocol specified the CABLIVI dose as 10 mg, to be delivered by withdrawing all of the reconstituted solution from the vial and administering the full amount. A dose recovery study showed that the mean dose that can be withdrawn from a vial is 11 mg. Therefore, based on the dose recovery study, the mean dose delivered in the trial was 11 mg.

The efficacy of CABLIVI in patients with aTTP was established based on time to platelet count response (platelet count ≥150,000/µL followed by cessation of daily plasma exchange within 5 days). Time to platelet count response was shorter among patients treated with CABLIVI, compared to placebo.

Figure 1: Platelet Response over Time

Treatment with CABLIVI resulted in a lower number of patients with TTP-related death, recurrence of TTP, or at least one treatment-emergent major thromboembolic event (a composite endpoint) during the treatment period (see Table 2).

Table 2: Patients in the HERCULES Study with aTTP-Related Death, a Recurrence of aTTP, or at Least One Treatment-Emergent Major Thromboembolic Event During Study Drug Treatment Period (ITT population)
Number of patients with | CABLIVI N=72 | Placebo N=73
Number of patients with | n (%) [Based on 71 patients who received at least one dose of study drug.] | n (%)
TTP-related death | 0 | 3 (4.1)
Recurrence of TTP (exacerbation) [Exacerbation defined as thrombocytopenia after initial recovery of platelet count (platelet count ≥150,000/µL with subsequent stop of daily plasma exchange within 5 days) that required reinitiation of daily plasma exchange during the 30-day post daily plasma exchange period.] | 3 (4.2) | 28 (38.4)
At least one treatment-emergent major thromboembolic event | 6 (8.5) | 6 (8.2)
Total [p<0.0001] | 9 (12.7) | 36 (49.3)
N = number of patients within the population of interest (by treatment group); n = number of patients with events;
TTP = thrombotic thrombocytopenic purpura; ITT = intent to treat.

The proportion of patients with a recurrence of TTP in the overall study period (the drug treatment period plus the 28-day follow-up period after discontinuation of drug treatment) was lower in the CABLIVI group (9/72 patients [13%]) compared to the placebo group (28/73 patients [38%] (p<0.001). In the 6 patients in the CABLIVI group who experienced a recurrence of TTP during the follow-up period (i.e., a relapse defined as recurrent thrombocytopenia after initial recovery of platelet count (platelet count ≥150,000/µL) that required reinitiation of daily plasma exchange, occurring after the 30-day post daily plasma exchange period), ADAMTS13 activity levels were <10% at the end of the study drug treatment, indicating that the underlying immunological disease was still active at the time CABLIVI was stopped.

16 HOW SUPPLIED/STORAGE AND HANDLING

16.1 How Supplied

CABLIVI (caplacizumab-yhdp) for injection is a sterile, white, preservative-free, lyophilized powder in a single-dose vial. Each carton (NDC 58468-0225-1) contains:

- one 11 mg CABLIVI single-dose vial (NDC 58468-0227-1)
- one 1 mL Sterile Water for Injection, USP, prefilled glass syringe (diluent for CABLIVI) (NDC 58468-0229-1)
- one sterile vial adapter
- one sterile hypodermic needle (30 gauge)
- two individually packaged alcohol swabs

16.2 Storage

Store refrigerated at 2°C to 8°C (36°F to 46°F) in the original carton to protect from light. Do not freeze. Unopened vials may be stored in the original carton at room temperature up to 30°C (86°F) for a single period of up to 2 months. Do not return CABLIVI to the refrigerator after it has been stored at room temperature.

17 PATIENT COUNSELING INFORMATION

Advise the patient to read the FDA-approved patient labeling (Instructions for Use).

Bleeding [see Warnings and Precautions (5.1)]

- Advise patients that bruising and bleeding may occur more easily, that nose bleeds and bleeding of gums may occur, and that it may take them longer than usual to stop bleeding.
- Advise patients to contact their healthcare provider immediately if symptoms of excessive bruising, excessive bleeding, or major bleeding occur. Signs and symptoms of bleeding include pain, swelling or discomfort, prolonged bleeding from cuts, increased menstrual flow or vaginal bleeding, nosebleeds, bleeding of gums from brushing, unusual bleeding or bruising, red or dark brown urine, red or tar black stools, headache, dizziness, or weakness [see Warnings and Precautions (5.1)].
- Advise patients to inform their healthcare provider before scheduling any elective surgery, dental procedure or other invasive interventions.

Manufactured by:
Ablynx N.V.
Technologiepark 21
9052 Ghent (Zwijnaarde), Belgium
A SANOFI COMPANY
U.S. License No. 2085

Distributed by:
Genzyme Corporation
Cambridge, MA 02141
A SANOFI COMPANY

For patent information: https://www.sanofi.us/en/products-and-resources/patents

CABLIVI is a registered trademark of Ablynx N.V., Belgium
©2024 Ablynx N.V. All rights reserved.

Instructions for Use
CABLIVI® (cab-LIV-ee)
(caplacizumab-yhdp)
for injection
Single-dose vial

Be sure that you read, understand, and follow this Instructions for Use before you inject CABLIVI and each time you get a refill. There may be new information. Your healthcare provider should show you how to prepare and inject CABLIVI properly before your first injection. Talk to your healthcare provider if you have any questions.

Important Information You Need to Know Before Injecting CABLIVI:

- Make sure that the name CABLIVI appears on the carton and vial label.
- For each injection, one CABLIVI carton is needed. Only use the vial one time.
- Only use the supplies that are provided in the carton to prepare your prescribed dose.
- Do not use CABLIVI after the expiration date on the carton.
- Do not reuse any of the supplies. After your injection, throw away (dispose of) the used vial with any remaining CABLIVI liquid in it. Throw away (dispose of) the used vial with the adapter attached and the syringe with the needle attached in an FDA-cleared sharps disposal container. See "Step 13: Throw away (dispose of) the used syringe and vial" at the end of this Instructions for Use for more disposal information.

How should I store CABLIVI?

- Store CABLIVI in the refrigerator between 36°F to 46°F (2°C to 8°C).
- Store CABLIVI in the original carton to protect from light.
- Do not freeze CABLIVI.
- Unopened CABLIVI vials may be stored at room temperature up to 86°F (30°C) in the original carton for a single period of up to two months. Write the date removed from the refrigerator in the space provided on the carton.
- Do not return CABLIVI to the refrigerator after it has been stored at room temperature.
- Use the mixed CABLIVI solution immediately. The mixed CABLIVI solution can be stored for up to 4 hours in the refrigerator at 36°F to 46°F (2°C to 8°C).
- Keep CABLIVI and all medicines out of the reach of children.

Each CABLIVI carton contains:

- 1 vial of CABLIVI
- 1 prefilled syringe containing 1 mL Sterile Water for Injection, USP (diluent for CABLIVI)
- 1 sterile vial adapter
- 1 sterile needle
- 2 alcohol swabs

Additional supplies needed:

- FDA-cleared sharps disposal container
- Cotton balls

Before preparing a dose of CABLIVI:

- Wash your hands well with soap and water.
- Prepare a clean flat surface.
- Check to make sure the carton contains all of the items needed to prepare a dose.
- Check the expiration date (See Figure A). Do not use CABLIVI if the date has passed.
- Do not use CABLIVI if the packaging or any supplies inside of the carton are damaged in any way.

Figure A

Step 1: Bring the vial and syringe to room temperature

- Place all the supplies in the carton on the clean flat surface.
- If the carton was not stored at room temperature, allow the vial and the syringe to reach room temperature by holding them in your hands for 10 seconds (See Figure B). Do not use any other way to warm up the vial and syringe.

Figure B

Step 2: Clean the rubber stopper

- Remove the green plastic flip-off cap from the metal cap of the vial (See Figure C). Do not use the vial if the green plastic cap is missing.

Figure C

- Clean the exposed rubber stopper using one alcohol swab to wipe it and allow it to dry for a few seconds (See Figure D).
- After cleaning the rubber stopper, do not touch it or allow it to touch any surface.

Figure D

Step 3: Attach the vial adapter

- Take the vial adapter and remove the paper cover (See Figure E). Leave the vial adapter in its opened plastic packaging for now. Do not touch the adapter itself.

Figure E

- Place the adapter over the vial, while keeping the adapter in its plastic packaging.
- Press down firmly on the adapter until it snaps into place, with the adapter spike pushing through the vial stopper (See Figure F). Do not remove the adapter from the vial once attached.
- Keep the adapter in its plastic packaging.

Figure F

Step 4: Prepare the syringe

- Pick up the syringe.
- While holding the syringe with one hand, break off the white plastic cap by snapping at the perforation of the cap with your other hand (See Figure G).
- Do not use the syringe if the white plastic cap is missing, loose, or damaged.
- Do not touch the syringe tip or allow it to come into contact with any surfaces.
- Lay the syringe on the clean flat surface.

Figure G

Step 5: Connect the syringe to adapter and vial

- Remove the plastic packaging from the adapter attached to the vial by holding the vial with one hand, pressing the sides of the adapter packaging with your other hand, and then lifting the packaging upwards (See Figure H).
- Be sure that the adapter does not detach from the vial.

Figure H

- Hold the adapter with the attached vial with one hand. Place the tip of the syringe on the connector part of the vial adapter using the other hand.
- Gently lock the syringe into the vial adapter by turning it clockwise until it cannot twist any further (See Figure I).

Figure I

Step 6: Prepare the solution

- Place the vial upright on the flat surface with the syringe pointing downwards.
- Slowly push the syringe plunger down until the syringe is empty (See Figure J). Do not remove the syringe from the vial adapter.

Figure J

- With the syringe still connected to the vial adapter, gently swirl the vial, with syringe attached, until the powder is dissolved in the vial (See Figure K). Do not shake the vial.

Figure K

- Allow the vial with the attached syringe to stand on the flat surface for 2 minutes at room temperature to allow the powder to completely dissolve (See Figure L). The plunger may rise up by itself again, this is normal.

Figure L

Step 7: Draw up solution

- Check the solution in the vial for particles, cloudiness, or clumps. All powder must be fully dissolved and the solution must be clear. Do not use the medicine if you see particles, cloudiness, or clumps. Use a new carton of CABLIVI or call your healthcare provider.
- Slowly press the syringe plunger fully down.
- Keep the syringe on the vial and turn the vial, adapter and syringe upside down.
- Slowly pull the plunger down to withdraw all of the solution from the vial into the syringe (See Figure M). Do not shake it.

Figure M

Step 8: Detach the syringe

- After drawing up the solution into the syringe, turn the vial, adapter and syringe back to the starting position and place on the flat surface (See Figure N).

Figure N

- Detach the filled syringe from the adapter by holding the vial and adapter in one hand and gently twisting the syringe counter-clockwise with the other hand (See Figure O).
- Throw away the vial and the attached adapter into a sharps disposal container.
- Do not touch the syringe tip or allow it to touch the clean flat surface. Place the syringe on the clean flat surface.

Figure O

Step 9: Attach the needle

- Open the needle package by using both thumbs to pull apart the packaging (See Figure P).
- Remove the needle from the package.

Figure P

- Attach the needle with the needle cap to the syringe by turning clockwise until it cannot twist any further (See Figure Q). Do not remove the needle cap.

Figure Q

- Pull back the needle safety shield (See Figure R).

Figure R

Step 10: Prepare your injection site

- Select an injection site on your stomach (abdomen) (See Figure S). Avoid the 2-inch area around your belly button (navel). It is important to avoid injecting in the same site on your abdomen that you used for a previous injection on consecutive days.

Figure S

- Clean your injection site with an alcohol swab (See Figure T). Let your skin dry.

Figure T

Step 11: Giving your injection

- Carefully remove the needle cap from the needle and throw it away in a sharps disposal container (See Figure U). Make sure the needle does not touch anything before the injection.

Figure U

- Hold the syringe at eye level with the needle pointing upwards.
- Check to see if there are any air bubbles. If there are any air bubbles, remove them by tapping the side of the syringe with your finger until they rise towards the tip (See Figure V).

Figure V

- Then, slowly push the plunger up until a small amount of liquid drips from the needle (See Figure W).

Figure W

- Gently use one hand to pinch the skin that has been cleaned between your thumb and forefinger, making a fold (See Figure X).
- Hold the pinch during the entire injection.

Figure X

- Use your other hand to insert the needle all the way into your skin fold at a 45 to 90-degree angle (See Figure Y).
- Push down on the plunger of the syringe until all of the solution is injected into your skin.
- Pull out the needle at the same angle you inserted it. Do not rub your injection site.

Figure Y

Step 12: After your injection

- Right after your injection, move the needle safety shield over the needle until it clicks into place to activate the shield (See Figure Z).
- In case you are bleeding at the injection site, place a cotton ball over the skin right away. Press gently on the cotton ball until the bleeding has stopped. If bleeding does not stop, call your healthcare provider.
- If your injection site becomes red or sore, call your healthcare provider right away.

Figure Z

Step 13: Throw away (dispose of) the used syringe and vial.

- Always throw away the syringe with the needle and the vial with the adapter in an FDA-cleared sharps disposal container right away after use. Do not throw away (dispose of) loose needles and syringes with your household trash.
- If you do not have an FDA-cleared sharps disposal container, you may use a household container that:
  - is made of a heavy-duty plastic,
  - can be closed with a tight-fitting, puncture-resistant lid, without sharps being able to come out,
  - is upright and stable during use,
  - is leak-resistant, and
  - is properly labeled to warn of hazardous waste inside the container.
- When your sharps disposal container is almost full, you will need to follow your community guidelines for the right way to dispose of your sharps disposal container. There may be state or local laws about how you should throw away used needles and syringes. For more information about safe sharps disposal, and for specific information about sharps disposal in the state in which you live, go to the FDA's website at: http://www.fda.gov/safesharpsdisposal.
- Do not dispose of your used sharps disposal container in your household trash unless your community guidelines permit this.
- Do not recycle your used sharps disposal container.

This Instructions for Use has been approved by the U.S. Food and Drug Administration.

Manufactured by:
Ablynx N.V.
Technologiepark 21
9052 Ghent (Zwijnaarde), Belgium
A SANOFI COMPANY
U.S. License No. 2085

Distributed by:
Genzyme Corporation
Cambridge, MA 02141
A SANOFI COMPANY

Revised October 2024

PRINCIPAL DISPLAY PANEL - Kit Carton

NDC 58468-0225-1
Rx only

Cablivi®
caplacizumab-yhdp
for Injection

For Intravenous and Subcutaneous Use

Must be reconstituted with diluent provided.

Single-dose vial. Discard unused portion.

Each carton contains:

- One 11 mg Cablivi single-dose vial
- One 1 mL Sterile Water for Injection, USP,
  prefilled glass syringe (diluent for Cablivi)
- One sterile vial adapter
- One sterile hypodermic needle (30 gauge)
- Two individually packaged alcohol swabs

11 mg

per vial

sanofi